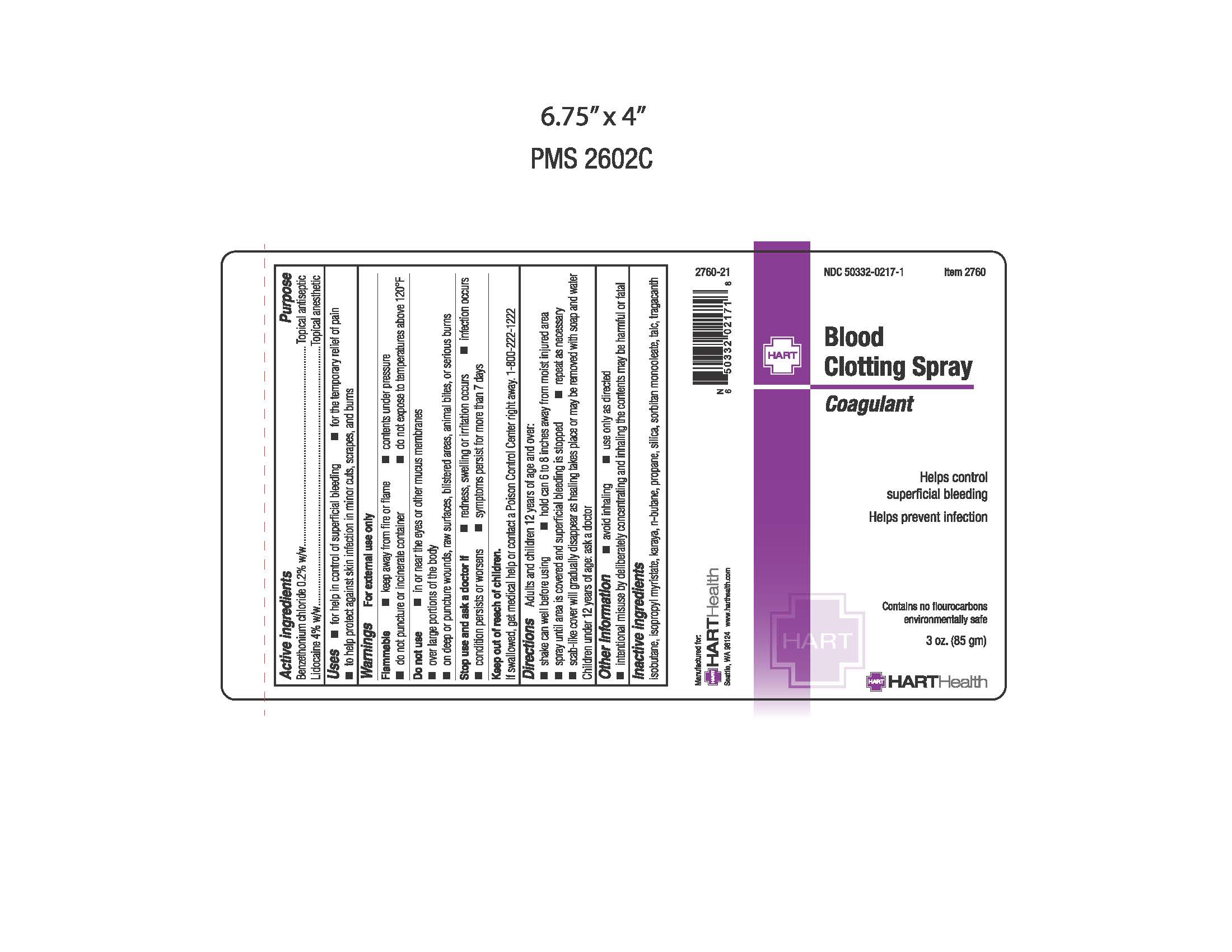 DRUG LABEL: Blood Clotting
NDC: 50332-0217 | Form: AEROSOL, SPRAY
Manufacturer: HART Health
Category: otc | Type: HUMAN OTC DRUG LABEL
Date: 20260114

ACTIVE INGREDIENTS: LIDOCAINE 3400 mg/85 g; BENZETHONIUM CHLORIDE 170 mg/85 g
INACTIVE INGREDIENTS: ISOBUTANE; ISOPROPYL MYRISTATE; KARAYA GUM; BUTANE; PROPANE; SILICON DIOXIDE; 3-(TRIETHOXYSILYL)PROPYLAMINE; SORBITAN MONOOLEATE; TALC; TRAGACANTH

Blood Clotting Spray

Active Ingredients

Benzethonium Chloride 0.2% w/w
Lidocaine 4% w/w

Purpose

Topical Antiseptic
Topical Anesthetic

Uses

- for help in control of superficial bleeding
- for the temporary relief of paid
- to help protect against skin infection in minor cuts, scrapes, and burns

Warnings

For external use only

Flammable

- keep away from flame
- contents under pressure
- do not puncture or incinerate container
- do not expose to temperatures above 120°F

Do not use

- in or near the eyes or other mucus membranes
- over large portions of the body
- on deep or puncture wounds, raw surfaces, blistered areas, animal bites, or serious burns

Stop use and ask doctor if

- redness, swelling, or irritation occurs
- infection occurs
- condition persists or worsens
- symptoms persist for more than 7 days

Keep out of reach of children.

If swallowed, get medical help or contact a Poison Control Center right away. 1-800-222-1222

Directions

Adults and children 23 years of age and over:

- shake can well before using
- hold 6-8 inches from moist injured area
- spray until area is covered and superficial bleeding is stopped
- repeat as necessary
- scab-like cover will gradually disappear as healing takes place or may be removed with soap and water

Children under 12 years of age: ask a doctor

Other Information

- avoid inhaling
- use only as directed
- intentional misuse by deliberately concentrating and inhaling the contents may be harmful or fatal

Inactive Ingredients

isobutane, isopropyl myristate, karaya, n-butane, propane, silica, sorbitan monooleate, talc, tragacanth